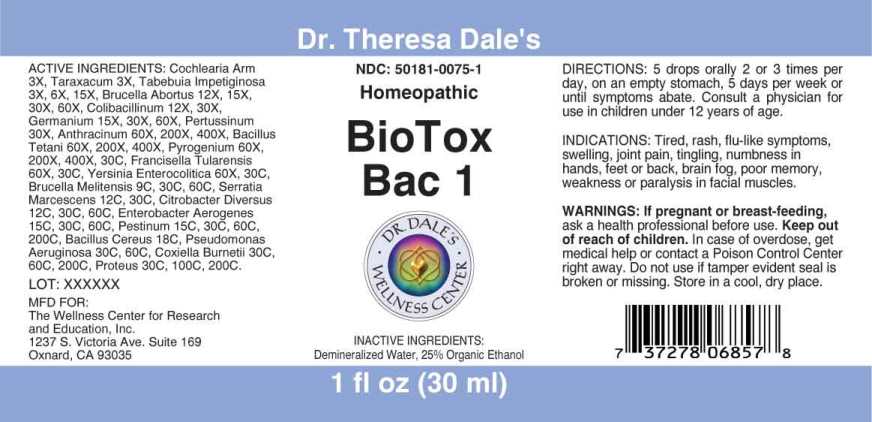 DRUG LABEL: BioTox Bac
NDC: 50181-0075 | Form: LIQUID
Manufacturer: The Wellness Center for Research
Category: homeopathic | Type: HUMAN OTC DRUG LABEL
Date: 20250606

ACTIVE INGREDIENTS: HORSERADISH 3 [hp_X]/1 mL; TARAXACUM OFFICINALE 3 [hp_X]/1 mL; TABEBUIA IMPETIGINOSA BARK 3 [hp_X]/1 mL; BRUCELLA ABORTUS 12 [hp_X]/1 mL; ESCHERICHIA COLI 12 [hp_X]/1 mL; GERMANIUM 15 [hp_X]/1 mL; HUMAN SPUTUM, BORDETELLA PERTUSSIS INFECTED 30 [hp_X]/1 mL; BACILLUS ANTHRACIS IMMUNOSERUM RABBIT 60 [hp_X]/1 mL; CLOSTRIDIUM TETANI 60 [hp_X]/1 mL; RANCID BEEF 60 [hp_X]/1 mL; FRANCISELLA TULARENSIS 60 [hp_X]/1 mL; YERSINIA ENTEROCOLITICA 60 [hp_X]/1 mL; BRUCELLA MELITENSIS 9 [hp_C]/1 mL; SERRATIA MARCESCENS 12 [hp_C]/1 mL; CITROBACTER KOSERI 12 [hp_C]/1 mL; ENTEROBACTER AEROGENES 15 [hp_C]/1 mL; YERSINIA PESTIS 15 [hp_C]/1 mL; BACILLUS CEREUS 18 [hp_C]/1 mL; PSEUDOMONAS AERUGINOSA 30 [hp_C]/1 mL; COXIELLA BURNETII 30 [hp_C]/1 mL; PROTEUS MIRABILIS 30 [hp_C]/1 mL
INACTIVE INGREDIENTS: WATER; ALCOHOL

DRUG FACTS:

ACTIVE INGREDIENTS:

Cochlearia Armoracia 3X, Taraxacum Officinale 3X, Tabebuia Impetiginosa 3X, 6X, 15X, Brucella Abortus 12X, 15X, 30X, 60X, Colibacillinum Cum Natrum Muriaticum 12X, 30X, Germanium 15X, 30X, 60X, Pertussinum 30X, Anthracinum 60X, 200X, 400X, Bacillus Tetani 60X, 200X, 400X, Pyrogenium 60X, 200X, 400X, 30C, Francisella Tularensis 60X, 30C, Yersinia Enterocolitica 60X, 30C, Brucella Melitensis 9C, 30C, 60C, Serratia Marcescenis 12C, 30C, Citrobacter Diversus 12C, 30C, 60C, Enterobacter Aerogenes 15C, 30C, 60C, Pestinum 15C, 30C, 60C, 200C, Bacillus Cereus 18C, Pseudomonas Aeruginosa 30C, 60C, Coxiella Burnetii 30C, 60C, 200C, Proteus (Mirabilis) 30C, 100C, 200C.

INDICATIONS:

Tired, rash, flu-like symptoms, swelling, joint pain, tingling, numbness in your hands, feet or back, brain fog, poor memory, weakness or paralysis in facial muscles.

WARINGS:

If pregnant or breast-feeding, ask a health professional before use.

Keep out of reach of children. In case of overdose, get medical help or contact a Poison Control Center right away.

Do not use if tamper evident seal is broken or missing.

Store in a cool, dry place.

Keep out of reach of children. In case of overdose, get medical help or contact a Poison Control Center right away.

DIRECTIONS:

5 drops orally 2 or 3 times per day, on an empty stomach, 5 days per week or until symptoms abate. Consult a physician for use in children under 12 years of age.

INDICATIONS:

Tired, rash, flu-like symptoms, swelling, joint pain, tingling, numbness in your hands, feet or back, brain fog, poor memory, weakness or paralysis in facial muscles.

INACTIVE INGREDIENTS:

Demineralized Water, 25% Organic Ethanol

QUESTIONS:

MFD FOR:

The Wellness Center for Research and Education, Inc.

1237 S. Victoria Ave. Suite 169

Oxnard, CA 93035

PACKAGE LABEL DISPLAY:

Dr. Theresa Dale's

NDC: 50181-0075-1

Homeopathic

BioTox Bac I

1 fl oz (30 ml)